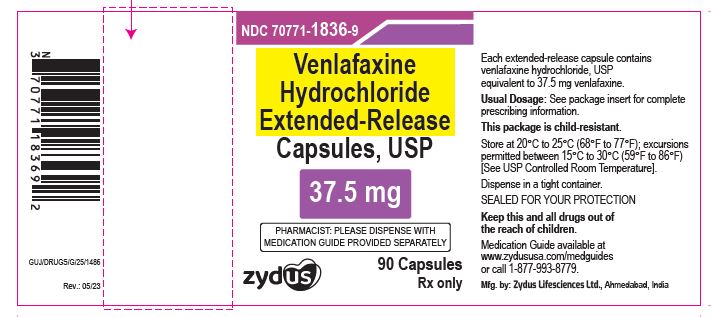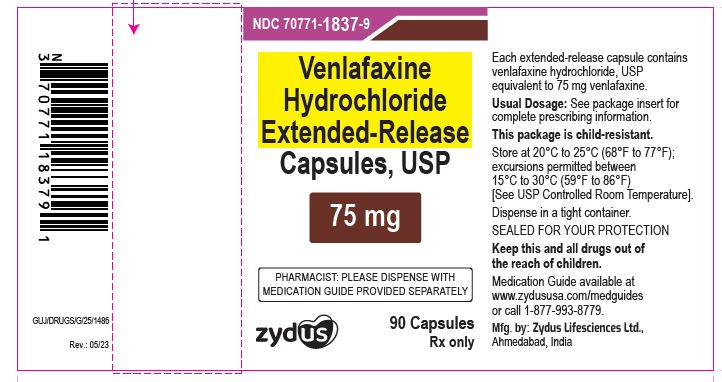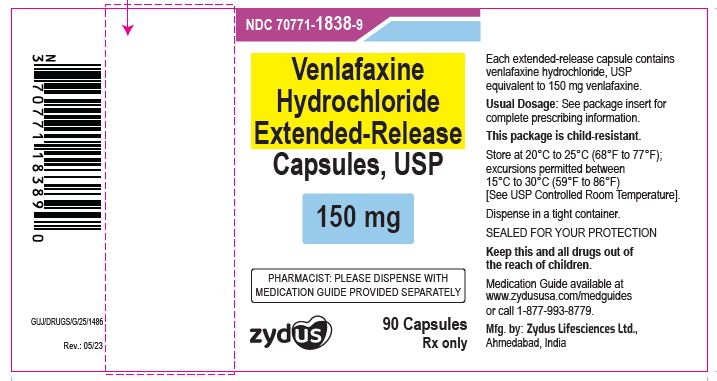 DRUG LABEL: Venlafaxine Hydrochloride
NDC: 70771-1836 | Form: CAPSULE, EXTENDED RELEASE
Manufacturer: Zydus Lifesciences Limited
Category: prescription | Type: HUMAN PRESCRIPTION DRUG LABEL
Date: 20230519

ACTIVE INGREDIENTS: VENLAFAXINE HYDROCHLORIDE 37.5 mg/1 1
INACTIVE INGREDIENTS: ETHYLCELLULOSE (7 MPA.S); FERROSOFERRIC OXIDE; GELATIN; HYPROMELLOSE 2910 (15 MPA.S); HYPROMELLOSE 2910 (5 MPA.S); MICROCRYSTALLINE CELLULOSE; POLYETHYLENE GLYCOL 8000; POTASSIUM HYDROXIDE; PROPYLENE GLYCOL; SHELLAC; SODIUM LAURYL SULFATE; TALC; TITANIUM DIOXIDE; WATER

VENLAFAXINE HYDROCHLORIDE EXTENDED-RELEASE CAPSULES

PACKAGE LABEL.PRINCIPAL DISPLAY PANEL

NDC 70771-1836-9

Venlafaxine Hydrochloride Extended-release Capsules USP, 37.5 mg

90 Capsules

Rx only

NDC 70771-1837-9

Venlafaxine Hydrochloride Extended-release Capsules USP, 75 mg

90 Capsules

Rx only

NDC 70771-1838-9

Venlafaxine Hydrochloride Extended-release Capsules USP, 150 mg

90 Capsules

Rx only